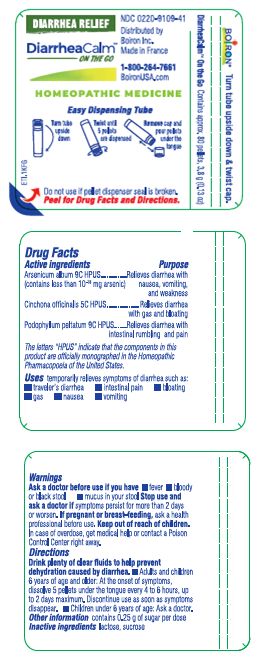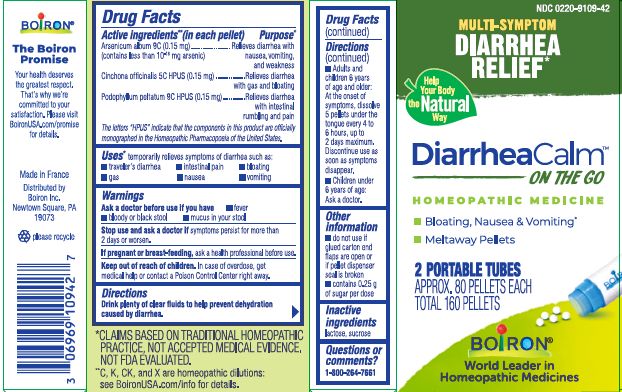 DRUG LABEL: DiarrheaCalm
NDC: 0220-9109 | Form: PELLET
Manufacturer: Boiron
Category: homeopathic | Type: HUMAN OTC DRUG LABEL
Date: 20250312

ACTIVE INGREDIENTS: PODOPHYLLUM 9 [hp_C]/1 1; CINCHONA OFFICINALIS BARK 5 [hp_C]/1 1; ARSENIC TRIOXIDE 9 [hp_C]/1 1
INACTIVE INGREDIENTS: SUCROSE; LACTOSE, UNSPECIFIED FORM

DiarrheaCalm pellets

Active ingredients** (in each pellet)

Arsenicum album 9C HPUS (0.15 mg)(contains less than 10^-18 mg arsenic)

Cinchona officinalis 5C HPUS (0.15 mg)

Podophyllum peltatum 9C HPUS (0.15 mg)

The letters "HPUS" indicate that the components in this product are officially monographed in the Homeopathic Pharmacopoeia of the United States.

Purpose*

Arsenicum album 9C HPUS (0.15 mg)………. Relieves diarrhea with nausea, vomiting, and weakness

Cinchona officinalis 5C HPUS (0.15 mg)……..………………………Relieves diarrhea with gas and bloating

Podophyllum peltatum 9C HPUS (0.15 mg)……Relieves diarrhea with intestinal rumbling and pain

The letters "HPUS" indicate that the components in this product are officially monographed in the Homeopathic Pharmacopoeia of the United States.

Uses*

temporarily relieves symptoms of diarrhea such as: ▪ traveler’s diarrhea ▪ intestinal pain ▪ bloating ▪ gas ▪ nausea ▪ vomiting

Ask a doctor before use if you have ▪ fever ▪ bloody or black stool ▪ mucus in your stool

Stop use and ask a doctor if symptoms persist for more than 2 days or worsen.

PREGNANCY OR BREAST FEEDING

If pregnant or breast-feeding, ask a health professional before use.

Keep out of reach of children. In case of overdose, get medical help or contact a Poison Control Center right away.

DOSAGE AND ADMINISTRATION

Drink plenty of clear fluids to help prevent dehydration caused by diarrhea.

▪ Adults and children 6 years of age and older: At the onset of symptoms, dissolve 5 pellets under the tongue every 4 to 6 hours, up to 2 days maximum. Discontinue use as soon as symptoms disappear.

▪ Children under 6 years of age: Ask a doctor.

INACTIVE INGREDIENT

lactose, sucrose

QUESTIONS

1-800-264-7661

Other information ▪ do not use if glued carton end flaps are open or if pellet dispenser seal is broken ▪ contains 0.25 g of sugar per dose

Do not use if pellet dispenser seal is broken.

MULTI-SYMPTOM DIARRHEA RELIEF*

Bloating, Nausea, Vomiting*

2 Portable tubes

Approx. 80 Pellets each, 3.8 g (0.13oz)

Total 160 pellets

Turn tube upside down

Twist until 5 pellets are dispensed

Turn tube upside down & twist cap

Distributed by

Boiron Inc.

Made in France

*CLAIMS BASED ON TRADITIONAL HOMEOPATHIC PRACTICE, NOT ACCEPTED MEDICAL EVIDENCE. NOT FDA EVALUATED.

**C, K, CK, and X are homeopathic dilutions: see BoironUSA.com/info for details.